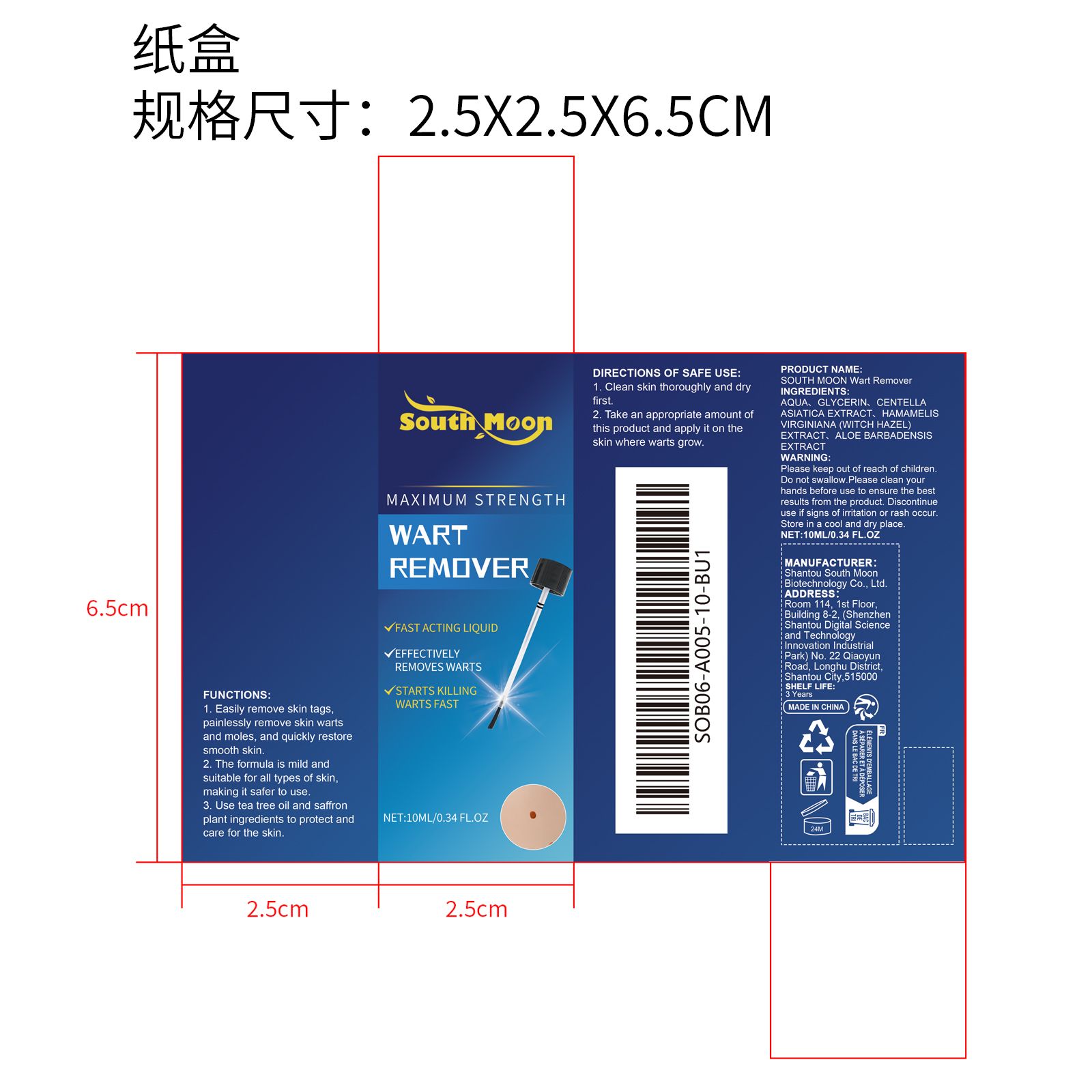 DRUG LABEL: SOUTH MOON Wart Remover
NDC: 84983-013 | Form: LIQUID
Manufacturer: Shantou South Moon Biotechnology Co., Ltd.
Category: otc | Type: HUMAN OTC DRUG LABEL
Date: 20251127

ACTIVE INGREDIENTS: CENTELLA ASIATICA TRITERPENOIDS 0.01 mg/10 mg; HAMAMELIS VIRGINIANA (WITCH HAZEL) LEAF WATER 0.002 mg/10 mg; ALOE BARBADENSIS LEAF 0.002 mg/10 mg
INACTIVE INGREDIENTS: AQUA 9.486 mg/10 mg; GLYCERIN 0.5 mg/10 mg

ACTIVE INGREDIENT

CENTELLA ASIATICA TRITERPENOIDS、HAMAMELIS VIRGINIANA LEAF WATER、ALOE BARBADENSIS LEAF

WHEN USING

1. Clean skin thoroughly and dry first

2. Take an appropriate amount of this product and apply it on the skin where warts grow.

PURPOSE

1. Easily remove skin tags, painlessly remove skin warts and moles, and quickly restore smooth skin.

2. The formula is mild and suitable for all types of skin, making it safer to use.

3. Use tea tree oil and saffron plant ingredients to protect and care for the skin.

WARNINGS

Please keep out of reach of children. Do not swallow.Please clean your hands before use to ensure the best results from the product. Discontinue use if signs of irritation or rash occur. Store in a cool and dry place.

DO NOT USE

Discontinue use if signs of irritation or rash occur.

STOP USE

Discontinue use if signs of irritation or rash occur.

KEEP OUT OF REACH OF CHILDREN

Please keep out of reach of children. Do not swallow.

STORAGE AND HANDLING

Store in a cool and dry place.

INACTIVE INGREDIENT

AQUA、GLYCERIN

DOSAGE AND ADMINISTRATION

1. Clean skin thoroughly and dry first

2. Take an appropriate amount of this product and apply it on the skin where warts grow.

INDICATIONS AND USAGE

Take an appropriate amount of this product and apply it on the skin where warts grow.